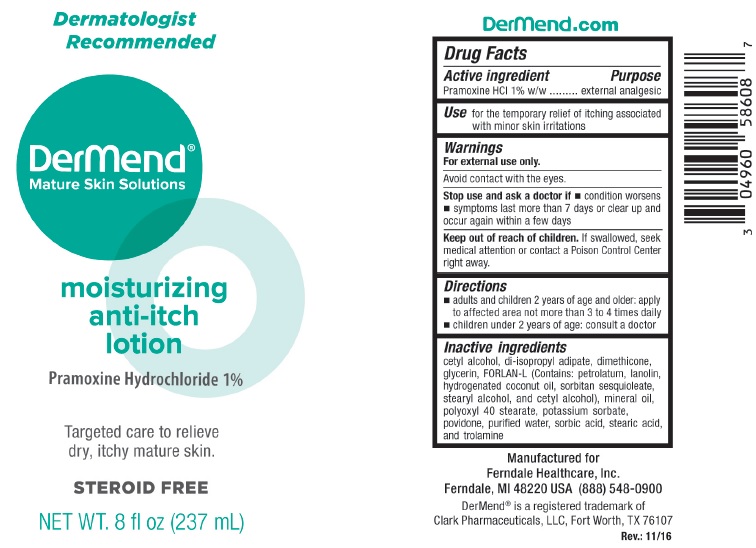 DRUG LABEL: DerMend Moisturizing Anti-Itch
NDC: 0496-0586 | Form: LOTION
Manufacturer: Ferndale Laboratories, Inc.
Category: otc | Type: HUMAN OTC DRUG LABEL
Date: 20241217

ACTIVE INGREDIENTS: PRAMOXINE HYDROCHLORIDE 10 mg/1 mL
INACTIVE INGREDIENTS: CETYL ALCOHOL; DIISOPROPYL ADIPATE; DIMETHICONE; GLYCERIN; PETROLATUM; LANOLIN; HYDROGENATED COCONUT OIL; SORBITAN SESQUIOLEATE; STEARYL ALCOHOL; MINERAL OIL; POLYOXYL 40 STEARATE; POTASSIUM SORBATE; POVIDONE; WATER; SORBIC ACID; STEARIC ACID; TROLAMINE

DerMend Moisturizing Anti-Itch Lotion

Active ingredient

Pramoxine HCl 1% w/w

Purpose

external analgesic

Use

for the temporary relief of itching associated with minor skin irritations

Warnings

For external use only.

Avoid contact with the eyes.

Stop use and ask a doctor if

- conditions worsens
- symptoms last more than 7 days or clear up and occur again within a few days

Keep out of reach of children.

If swallowed, seek medical attention or contact a Poison Cotrol Center right away.

Directions

- adults and children 2 years of age and older: apply to affected area not more than 3 to 4 times daily
- children under 2 years of age: consult a doctor

Inactive ingredients

cetyl alcohol, di-isopropyl adipate, dimethicone, glycerin, FORLAN-L (Contains: petrolatum, lanolin, hydrogenated coconut oil, sorbitan sesquioleate, stearyl alcohol, and cetyl alcohol), mineral oil, polyoxyl 40 stearate, potassium sorbate, povidone, purified water, sorbic acid, stearic acid, and trolamine

Package Label

NDC 0496-0586-08

8oz (237mL)